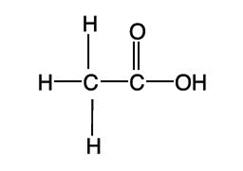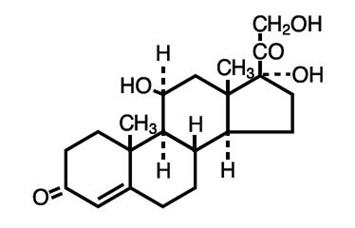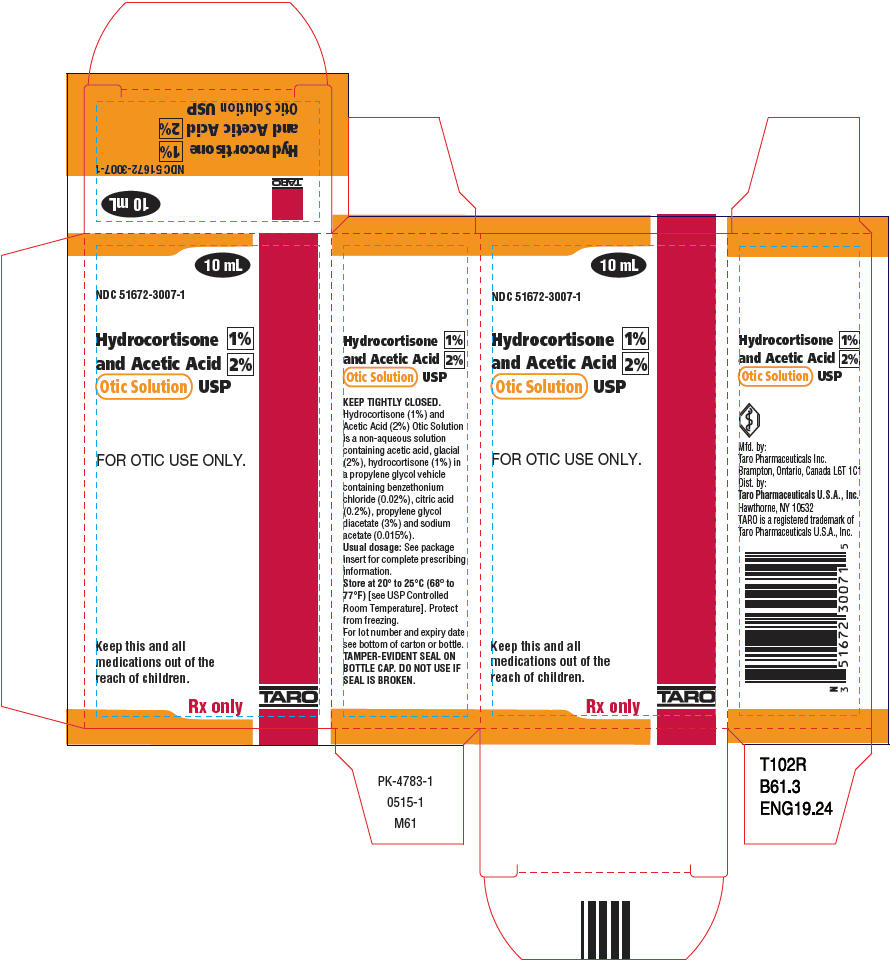 DRUG LABEL: Hydrocortisone and Acetic Acid
NDC: 51672-3007 | Form: SOLUTION
Manufacturer: Sun Pharmaceutical Industries, Inc.
Category: prescription | Type: HUMAN PRESCRIPTION DRUG LABEL
Date: 20250707

ACTIVE INGREDIENTS: HYDROCORTISONE 10.4 mg/1 mL; ACETIC ACID 20.8 mg/1 mL
INACTIVE INGREDIENTS: SODIUM ACETATE; ANHYDROUS CITRIC ACID; PROPYLENE GLYCOL; PROPYLENE GLYCOL DIACETATE; BENZETHONIUM CHLORIDE

Hydrocortisone 1%
and Acetic Acid 2%
Otic Solution

(Hydrocortisone and Acetic Acid Otic Solution, USP)

Rx only

DESCRIPTION

Hydrocortisone and Acetic Acid Otic Solution, USP contains Hydrocortisone (1%) and acetic acid, glacial (2%) in a propylene glycol vehicle containing benzethonium chloride (0.02%), citric acid (0.2%), propylene glycol diacetate (3%) and sodium acetate (0.015%).

Acetic acid has a molecular formula of CH3COOH with molecular weight of 60.05. The structural formula is:

Hydrocortisone is a Synthetic Steroid used as an anti-inflammatory and antipruritic agent. Its chemical name is Pregn-4-ene-3,20-dione, 11, 17, 21-trihydroxy-, (11β)-. Hydrocortisone has a molecular formula of C21H30O5with molecular weight 362.46. The structural formula is:

Hydrocortisone and acetic acid is available as a non-aqueous otic solution buffered at pH (2.0 to 4.0) for use in the external ear canal.

CLINICAL PHARMACOLOGY

Acetic acid is anti-bacterial and antifungal; hydrocortisone is anti-inflammatory, antiallergic and antipruritic; propylene glycol is hydrophilic and provides a low surface tension; benzethonium chloride is a surface active agent that promotes contact of the solution with tissues.

INDICATIONS AND USAGE

For the treatment of superficial infections of the external auditory canal caused by organisms susceptible to the action of the antimicrobial, complicated by inflammation.

CONTRAINDICATIONS

Hypersensitivity to hydrocortisone and acetic acid otic solution or any of the ingredients; herpes simplex, vaccinia and varicella. Perforated tympanic membrane is considered a contraindication to the use of any medication in the external ear canal.

WARNINGS

Discontinue promptly if sensitization or irritation occurs.

PRECAUTIONS

Transient stinging or burning may be noted occasionally when the solution is first instilled into the acutely inflamed ear.

Pediatric Use

Safety and effectiveness in pediatric patients below the age of 3 years have not been established.

ADVERSE REACTIONS

Stinging or burning may be noted occasionally; local irritation has occurred very rarely.

DOSAGE AND ADMINISTRATION

Carefully remove all cerumen and debris to allow hydrocortisone 1% and acetic acid 2% otic solution to contact infected surfaces directly. To promote continuous contact, insert a wick of cotton saturated with the solution into the ear canal; the wick may also be saturated after insertion. Instruct the patient to keep the wick in for at least 24 hours and to keep it moist by adding 3 to 5 drops of the solution every 4 to 6 hours. The wick may be removed after 24 hours but the patient should continue to instill 5 drops 3 or 4 times daily thereafter, for as long as indicated. In pediatric patients, 3 to 4 drops may be sufficient due to the smaller capacity of the ear canal.

HOW SUPPLIED

Hydrocortisone 1% and acetic acid 2% otic solution is available in 10 mL plastic, controlled dropper tip bottle.

10 mL bottle | NDC 51672-3007-1

STORAGE AND HANDLING

Store at 20° to 25°C (68° to 77°F)[see USP Controlled Room Temperature]. Protect from freezing. Keep container tightly closed.

Mfd. by: Taro Pharmaceuticals Inc.
Brampton, Ontario, Canada L6T 1C1
Dist. by: Taro Pharmaceuticals U.S.A., Inc.
Hawthorne, NY 10532

Revised: May, 2015

PK-4785-1
61
0515-1

PRINCIPAL DISPLAY PANEL - 10 mL Bottle Carton

10 mL

NDC 51672-3007-1

Hydrocortisone 1%
and Acetic Acid 2%
Otic Solution USP

FOR OTIC USE ONLY.

Keep this and all
medications out of the
reach of children.

Rx only

TARO